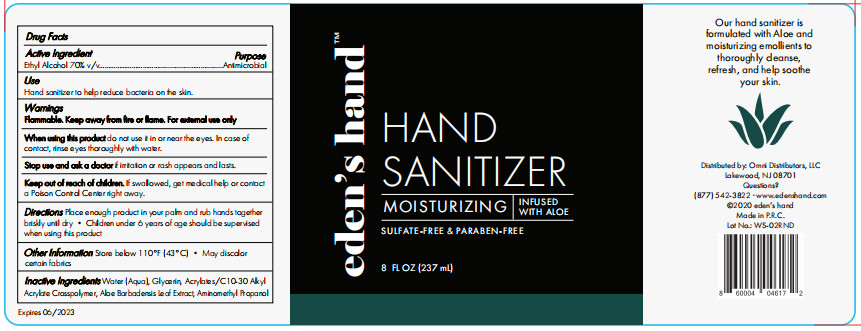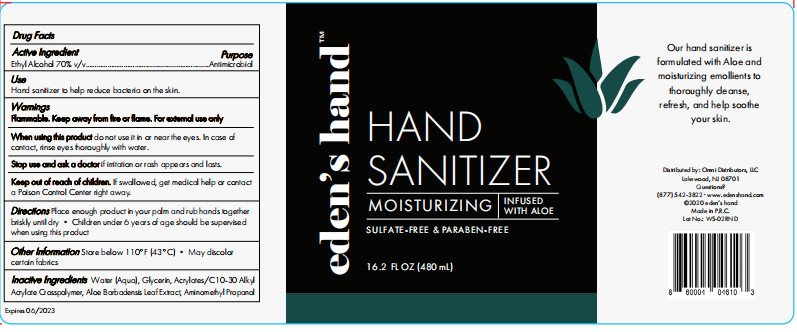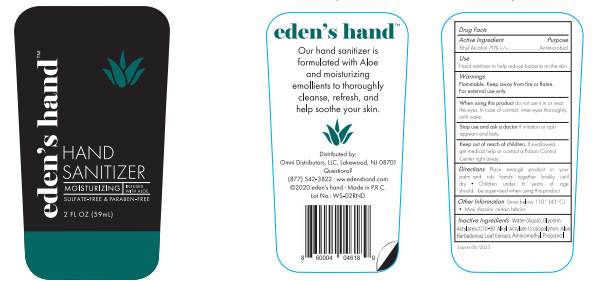 DRUG LABEL: Hand Sanitizer
NDC: 75541-009 | Form: GEL
Manufacturer: Ningbo Meiteli Cosmetic Co., Ltd.
Category: otc | Type: HUMAN OTC DRUG LABEL
Date: 20200615

ACTIVE INGREDIENTS: ALCOHOL 70 mL/100 mL
INACTIVE INGREDIENTS: AMINOMETHYLPROPANOL; GLYCERIN; WATER; ALOE VERA LEAF; CARBOMER COPOLYMER TYPE A (ALLYL PENTAERYTHRITOL CROSSLINKED)

Hand Sanitizer

Active Ingredient(s)

Alcohol 70% v/v

Purpose

antibacterial

Use

Hand Sanitizer to help reduce BACIERTA on the skin

Warning

Flammable. Keep away from heat or flame For external use only.

Do not use near eyes

Do not use with children under the age of 2 months
on open skin wounds When using this product

Stop use

Stop use and ask a doctor If irritation or rash appears occurs.

Keep out of reach of children

If swallowed get medical help or contact a poic conitd center rigth away

Directions

Place enough product in your palm and rub hands together briskly until dry
children under 6 years of age should be supervised when using this produc

Other

- Store bela 111F(43C) May dislor cetain fabrics

Inactive ingredients

Water(Aqua), Glycerin, Acrylates/C10-30 Alkyl Acrylate Crosspolymer, Aloe Barbadensis Leaf Extract, Aminomethyl Propanol

Do not use it in or near the eyes. In case of contact with eyes,rinse eyes thoroughly with water.